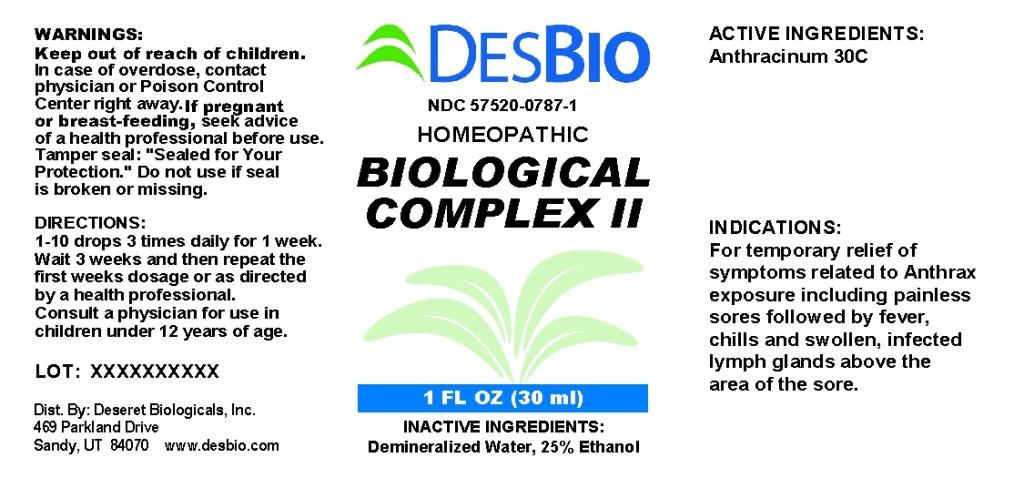 DRUG LABEL: Biological Complex
NDC: 57520-0787 | Form: LIQUID
Manufacturer: Apotheca Company
Category: homeopathic | Type: HUMAN OTC DRUG LABEL
Date: 20110826

ACTIVE INGREDIENTS: BACILLUS ANTHRACIS IMMUNOSERUM RABBIT 30 [hp_C]/1 mL
INACTIVE INGREDIENTS: WATER; ALCOHOL

Biological Complex II

ACTIVE INGREDIENTS: Anthracinum 30C.

PURPOSE

INDICATIONS: For temporary relief of symptoms related to Anthrax exposure including painless sores followed by fever, chills and swollen, infected lymph glands above the area of the sore.

WARNINGS

WARNINGS: Keep out of reach of children. In case of overdose, contact physician or Poison Control Center right away.

If pregnant or breast-feeding, seek advice of a health professional before use.

Tamper seal: "Sealed for Your Protection." Do not use if seal is broken or missing.

DOSAGE AND ADMINISTRATION

DIRECTIONS: 1-10 drops 3 times daily for 1 week. Wait 3 weeks and then repeat the first weeks dosage or as directed by a health professional. Consult a physician for use in children under 12 years of age.

INACTIVE INGREDIENTS: Demineralized water, 25% Ethanol.

KEEP OUT OF REACH OF CHILDREN. In case of overdose, contact physician or Poison Control Center right away.

INDICATIONS AND USAGE

INDICATIONS: For temporary relief of symptoms related to Anthrax exposure including painless sores followed by fever, chills and swollen, infected lymph glands above the area of the sore.

QUESTIONS

Dist. By:

Deseret Biologicals, Inc.

469 Parkland Drive

Sandy, UT 84070

www.desbio.com

PACKAGE LABEL

DESBIO

NDC 57520-0787-1

HOMEOPATHIC

BIOLOGICAL COMPLEX II

1 FL OZ (30 ml)